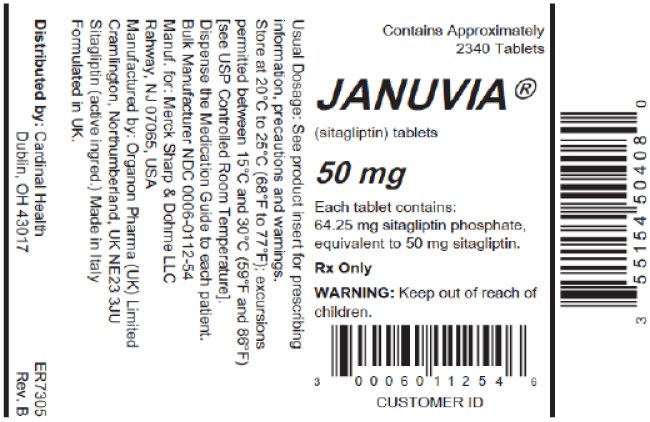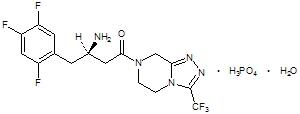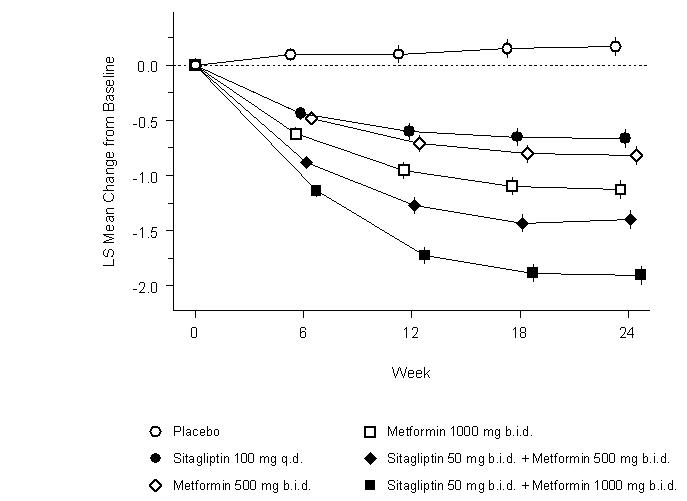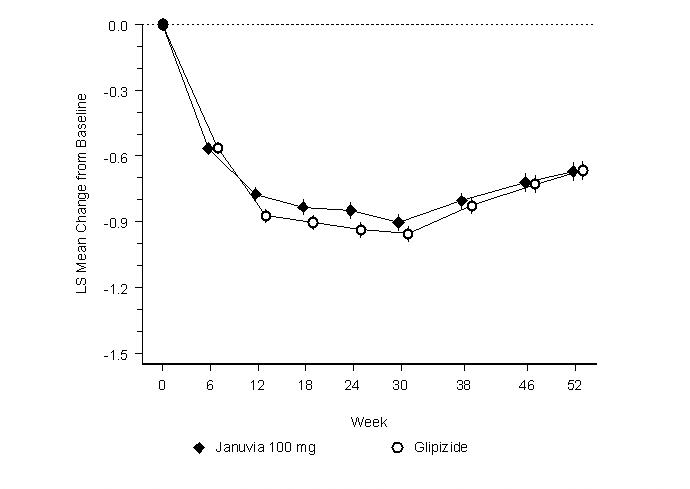 DRUG LABEL: JANUVIA
NDC: 55154-5040 | Form: TABLET, FILM COATED
Manufacturer: Cardinal Health 107, LLC
Category: prescription | Type: HUMAN PRESCRIPTION DRUG LABEL
Date: 20251105

ACTIVE INGREDIENTS: SITAGLIPTIN PHOSPHATE 50 mg/1 1
INACTIVE INGREDIENTS: MICROCRYSTALLINE CELLULOSE; ANHYDROUS DIBASIC CALCIUM PHOSPHATE; CROSCARMELLOSE SODIUM; MAGNESIUM STEARATE; SODIUM STEARYL FUMARATE; PROPYL GALLATE; POLYVINYL ALCOHOL, UNSPECIFIED; POLYETHYLENE GLYCOL, UNSPECIFIED; TALC; TITANIUM DIOXIDE; FERRIC OXIDE RED; FERRIC OXIDE YELLOW

HIGHLIGHTS OF PRESCRIBING INFORMATION

These highlights do not include all the information needed to use JANUVIA safely and effectively. See full prescribing information for JANUVIA.
JANUVIA® (sitagliptin) tablets, for oral use
Initial U.S. Approval: 2006

1 INDICATIONS AND USAGE

JANUVIA is a dipeptidyl peptidase-4 (DPP-4) inhibitor indicated as an adjunct to diet and exercise to improve glycemic control in adults with type 2 diabetes mellitus. (1)

Limitations of Use:

- JANUVIA should not be used in patients with type 1 diabetes (1)
- JANUVIA has not been studied in patients with a history of pancreatitis. (1, 5.1)

2 DOSAGE AND ADMINISTRATION

The recommended dose of JANUVIA is 100 mg once daily. JANUVIA can be taken with or without food. (2.1)

Dosage adjustment is recommended for patients with eGFR less than 45 mL/min/1.73 m^2. (2.2)

Dosage Adjustment in Patients with Renal Impairment (2.2)
eGFR greater than or equal to 30 mL/min/1.73 m^2 to less than 45 mL/min/1.73 m^2 | eGFR less than 30 mL/min/1.73 m^2 (including patients with end stage renal disease [ESRD] on dialysis)
50 mg once daily | 25 mg once daily

3 DOSAGE FORMS AND STRENGTHS

Tablets: 100 mg, 50 mg, and 25 mg (3)

4 CONTRAINDICATIONS

History of a serious hypersensitivity reaction to sitagliptin, such as anaphylaxis or angioedema (5.5, 6.2)

5 WARNINGS AND PRECAUTIONS

- Pancreatitis: There have been postmarketing reports of acute pancreatitis, including fatal and non-fatal hemorrhagic or necrotizing pancreatitis. If pancreatitis is suspected, promptly discontinue JANUVIA. (5.1)
- Heart failure: Heart failure has been observed with two other members of the DPP-4 inhibitor class. Consider risks and benefits of JANUVIA in patients who have known risk factors for heart failure. Monitor patients for signs and symptoms. (5.2)
- Acute Renal Failure: Has been reported postmarketing, sometimes requiring dialysis. Assessment of renal function is recommended prior to initiating JANUVIA and periodically thereafter. (5.3)
- Hypoglycemia with Concomitant Use with Insulin or Insulin Secretagogues: Increased risk of hypoglycemia when used in combination with insulin and/or an insulin secretagogue. Lower dose of insulin or insulin secretagogue may be required. (5.4, 7.1)
- Hypersensitivity Reactions: There have been postmarketing reports of serious allergic and hypersensitivity reactions in patients treated with JANUVIA such as anaphylaxis, angioedema, and exfoliative skin conditions including Stevens-Johnson syndrome. Promptly stop JANUVIA, assess for other potential causes, institute appropriate monitoring and treatment. (5.5, 6.2)
- Severe and Disabling Arthralgia: Has been reported in patients taking DPP-4 inhibitors. Consider as a possible cause for severe joint pain and discontinue drug if appropriate. (5.6)
- Bullous Pemphigoid: There have been postmarketing reports requiring hospitalization in patients taking DPP-4 inhibitors. Tell patients to report development of blisters or erosions. If bullous pemphigoid is suspected, discontinue JANUVIA. (5.7)

6 ADVERSE REACTIONS

Adverse reactions reported in ≥5% of patients treated with JANUVIA and more commonly than in patients treated with placebo are: upper respiratory tract infection, nasopharyngitis and headache. In the add-on to sulfonylurea and add-on to insulin studies, hypoglycemia was also more commonly reported in patients treated with JANUVIA compared to placebo. (6.1)

To report SUSPECTED ADVERSE REACTIONS, contact Merck Sharp & Dohme LLC at 1-877-888-4231 or FDA at 1-800-FDA-1088 or www.fda.gov/medwatch.

FULL PRESCRIBING INFORMATION

1 INDICATIONS AND USAGE

JANUVIA® is indicated as an adjunct to diet and exercise to improve glycemic control in adults with type 2 diabetes mellitus.

Limitations of Use

JANUVIA should not be used in patients with type 1 diabetes.

JANUVIA has not been studied in patients with a history of pancreatitis. It is unknown whether patients with a history of pancreatitis are at increased risk for the development of pancreatitis while using JANUVIA. [See Warnings and Precautions (5.1).]

2 DOSAGE AND ADMINISTRATION

2.1 Recommended Dosing

The recommended dose of JANUVIA is 100 mg once daily. JANUVIA can be taken with or without food.

2.2 Recommendations for Use in Renal Impairment

Assess renal function prior to initiation of JANUVIA and periodically thereafter.

For patients with an estimated glomerular filtration rate [eGFR] greater than or equal to 45 mL/min/1.73 m^2 to less than 90 mL/min/1.73 m^2, no dosage adjustment for JANUVIA is required.

For patients with moderate renal impairment (eGFR greater than or equal to 30 mL/min/1.73 m^2 to less than 45 mL/min/1.73 m^2), the dose of JANUVIA is 50 mg once daily.

For patients with severe renal impairment (eGFR less than 30 mL/min/1.73 m^2) or with end-stage renal disease (ESRD) requiring hemodialysis or peritoneal dialysis, the dose of JANUVIA is 25 mg once daily. JANUVIA may be administered without regard to the timing of dialysis.

3 DOSAGE FORMS AND STRENGTHS

- 100 mg tablets are beige, round, film-coated tablets with "277" on one side.
- 50 mg tablets are light beige, round, film-coated tablets with "112" on one side.
- 25 mg tablets are pink, round, film-coated tablets with "221" on one side.

4 CONTRAINDICATIONS

History of a serious hypersensitivity reaction to sitagliptin, such as anaphylaxis or angioedema. [See Warnings and Precautions (5.5); Adverse Reactions (6.2).]

5 WARNINGS AND PRECAUTIONS

5.1 Pancreatitis

There have been postmarketing reports of acute pancreatitis, including fatal and non-fatal hemorrhagic or necrotizing pancreatitis, in patients taking JANUVIA. After initiation of JANUVIA, patients should be observed carefully for signs and symptoms of pancreatitis. If pancreatitis is suspected, JANUVIA should promptly be discontinued and appropriate management should be initiated. It is unknown whether patients with a history of pancreatitis are at increased risk for the development of pancreatitis while using JANUVIA.

5.2 Heart Failure

An association between dipeptidyl peptidase-4 (DPP-4) inhibitor treatment and heart failure has been observed in cardiovascular outcomes trials for two other members of the DPP-4 inhibitor class. These trials evaluated patients with type 2 diabetes mellitus and atherosclerotic cardiovascular disease.

Consider the risks and benefits of JANUVIA prior to initiating treatment in patients at risk for heart failure, such as those with a prior history of heart failure and a history of renal impairment, and observe these patients for signs and symptoms of heart failure during therapy. Advise patients of the characteristic symptoms of heart failure and to immediately report such symptoms. If heart failure develops, evaluate and manage according to current standards of care and consider discontinuation of JANUVIA.

5.3 Acute Renal Failure

There have been postmarketing reports of worsening renal function, including acute renal failure, sometimes requiring dialysis. A subset of these reports involved patients with renal impairment, some of whom were prescribed inappropriate doses of sitagliptin. A return to baseline levels of renal impairment has been observed with supportive treatment and discontinuation of potentially causative agents. Consideration can be given to cautiously reinitiating JANUVIA if another etiology is deemed likely to have precipitated the acute worsening of renal function.

Assessment of renal function is recommended prior to initiating JANUVIA and periodically thereafter. A dosage adjustment is recommended in patients with moderate or severe renal impairment and in patients with ESRD requiring hemodialysis or peritoneal dialysis. [See Dosage and Administration (2.2); Use in Specific Populations (8.6).]

5.4 Hypoglycemia with Concomitant Use with Insulin or Insulin Secretagogues

When JANUVIA was used in combination with insulin or insulin secretagogues (e.g., sulfonylurea), medications known to cause hypoglycemia, the incidence of hypoglycemia was increased over that of placebo used in combination with a sulfonylurea or with insulin. [See Adverse Reactions (6.1).] Therefore, a lower dose of sulfonylurea or insulin may be required to reduce the risk of hypoglycemia. [See Drug Interactions (7.1).]

5.5 Hypersensitivity Reactions

There have been postmarketing reports of serious hypersensitivity reactions in patients treated with JANUVIA. These reactions include anaphylaxis, angioedema, and exfoliative skin conditions including Stevens-Johnson syndrome. Onset of these reactions occurred within the first 3 months after initiation of treatment with JANUVIA, with some reports occurring after the first dose. If a hypersensitivity reaction is suspected, discontinue JANUVIA, assess for other potential causes for the event, and institute alternative treatment for diabetes. [See Adverse Reactions (6.2).]

Angioedema has also been reported with other DPP-4 inhibitors. Use caution in a patient with a history of angioedema with another DPP-4 inhibitor because it is unknown whether such patients will be predisposed to angioedema with JANUVIA.

5.6 Severe and Disabling Arthralgia

There have been postmarketing reports of severe and disabling arthralgia in patients taking DPP-4 inhibitors. The time to onset of symptoms following initiation of drug therapy varied from one day to years. Patients experienced relief of symptoms upon discontinuation of the medication. A subset of patients experienced a recurrence of symptoms when restarting the same drug or a different DPP-4 inhibitor. Consider DPP-4 inhibitors as a possible cause for severe joint pain and discontinue drug if appropriate.

5.7 Bullous Pemphigoid

Postmarketing cases of bullous pemphigoid requiring hospitalization have been reported with DPP-4 inhibitor use. In reported cases, patients typically recovered with topical or systemic immunosuppressive treatment and discontinuation of the DPP-4 inhibitor. Tell patients to report development of blisters or erosions while receiving JANUVIA. If bullous pemphigoid is suspected, JANUVIA should be discontinued and referral to a dermatologist should be considered for diagnosis and appropriate treatment.

6 ADVERSE REACTIONS

The following adverse reactions are also discussed elsewhere in the labeling:

- Pancreatitis [see Warnings and Precautions (5.1)]
- Heart Failure [see Warnings and Precautions (5.2)]
- Acute Renal Failure [see Warnings and Precautions (5.3)]
- Hypoglycemia with Concomitant Use with Insulin or Insulin Secretagogues [see Warnings and Precautions (5.4)]
- Hypersensitivity Reactions [see Warnings and Precautions (5.5)]
- Severe and Disabling Arthralgia [see Warnings and Precautions (5.6)]
- Bullous Pemphigoid [see Warnings and Precautions (5.7)]

6.1 Clinical Trials Experience

Because clinical trials are conducted under widely varying conditions, adverse reaction rates observed in the clinical trials of a drug cannot be directly compared to rates in the clinical trials of another drug and may not reflect the rates observed in practice.

In controlled clinical studies as both monotherapy and combination therapy with metformin, pioglitazone, or rosiglitazone and metformin, the overall incidence of adverse reactions, hypoglycemia, and discontinuation of therapy due to clinical adverse reactions with JANUVIA were similar to placebo. In combination with glimepiride, with or without metformin, the overall incidence of clinical adverse reactions with JANUVIA was higher than with placebo, in part related to a higher incidence of hypoglycemia (see Table 3); the incidence of discontinuation due to clinical adverse reactions was similar to placebo.

Two placebo-controlled monotherapy studies, one of 18- and one of 24-week duration, included patients treated with JANUVIA 100 mg daily, JANUVIA 200 mg daily, and placebo. Five placebo-controlled add-on combination therapy studies were also conducted: one with metformin; one with pioglitazone; one with metformin and rosiglitazone; one with glimepiride (with or without metformin); and one with insulin (with or without metformin). In these trials, patients with inadequate glycemic control on a stable dose of the background therapy were randomized to add-on therapy with JANUVIA 100 mg daily or placebo. The adverse reactions, excluding hypoglycemia, reported regardless of investigator assessment of causality in ≥5% of patients treated with JANUVIA 100 mg daily and more commonly than in patients treated with placebo, are shown in Table 1 for the clinical trials of at least 18 weeks duration. Incidences of hypoglycemia are shown in Table 3.

Table 1: Placebo-Controlled Clinical Studies of JANUVIA Monotherapy or Add-on Combination Therapy with Pioglitazone, Metformin + Rosiglitazone, or Glimepiride +/- Metformin: Adverse Reactions (Excluding Hypoglycemia) Reported in ≥5% of Patients and More Commonly than in Patients Given Placebo, Regardless of Investigator Assessment of Causality [Intent-to-treat population]
 | Number of Patients (%)
Monotherapy (18 or 24 weeks) | JANUVIA 100 mg | Placebo
 | N = 443 | N = 363
Nasopharyngitis | 23 (5.2) | 12 (3.3)
Combination with Pioglitazone (24 weeks) | JANUVIA 100 mg +; Pioglitazone | Placebo +; Pioglitazone
 | N = 175 | N = 178
Upper Respiratory Tract Infection | 11 (6.3) | 6 (3.4)
Headache | 9 (5.1) | 7 (3.9)
Combination with Metformin + Rosiglitazone (18 weeks) | JANUVIA 100 mg; + Metformin + Rosiglitazone | Placebo; + Metformin + Rosiglitazone
 | N = 181 | N = 97
Upper Respiratory Tract Infection | 10 (5.5) | 5 (5.2)
Nasopharyngitis | 11 (6.1) | 4 (4.1)
Combination with Glimepiride (+/- Metformin) (24 weeks) | JANUVIA 100 mg; + Glimepiride; (+/- Metformin) | Placebo; + Glimepiride; (+/- Metformin)
 | N = 222 | N = 219
Nasopharyngitis | 14 (6.3) | 10 (4.6)
Headache | 13 (5.9) | 5 (2.3)

In the 24-week study of patients receiving JANUVIA as add-on combination therapy with metformin, there were no adverse reactions reported regardless of investigator assessment of causality in ≥5% of patients and more commonly than in patients given placebo.

In the 24-week study of patients receiving JANUVIA as add-on therapy to insulin (with or without metformin), there were no adverse reactions reported regardless of investigator assessment of causality in ≥5% of patients and more commonly than in patients given placebo, except for hypoglycemia (see Table 3).

In the study of JANUVIA as add-on combination therapy with metformin and rosiglitazone (Table 1), through Week 54 the adverse reactions reported regardless of investigator assessment of causality in ≥5% of patients treated with JANUVIA and more commonly than in patients treated with placebo were: upper respiratory tract infection (JANUVIA, 15.5%; placebo, 6.2%), nasopharyngitis (11.0%, 9.3%), peripheral edema (8.3%, 5.2%), and headache (5.5%, 4.1%).

In a pooled analysis of the two monotherapy studies, the add-on to metformin study, and the add-on to pioglitazone study, the incidence of selected gastrointestinal adverse reactions in patients treated with JANUVIA was as follows: abdominal pain (JANUVIA 100 mg, 2.3%; placebo, 2.1%), nausea (1.4%, 0.6%), and diarrhea (3.0%, 2.3%).

In an additional, 24-week, placebo-controlled factorial study of initial therapy with sitagliptin in combination with metformin, the adverse reactions reported (regardless of investigator assessment of causality) in ≥5% of patients are shown in Table 2.

Table 2: Initial Therapy with Combination of Sitagliptin and Metformin: Adverse Reactions Reported (Regardless of Investigator Assessment of Causality) in ≥5% of Patients Receiving Combination Therapy (and Greater than in Patients Receiving Metformin alone, Sitagliptin alone, and Placebo) [Intent-to-treat population.]
 | Number of Patients (%)
 | Placebo | Sitagliptin; (JANUVIA) 100 mg QD | Metformin HCl; 500 or 1000 mg bid [Data pooled for the patients given the lower and higher doses of metformin.] | Sitagliptin; 50 mg bid +; Metformin HCl; 500 or 1000 mg bid
 | N = 176 | N = 179 | N = 364 | N = 372
Upper Respiratory Infection | 9 (5.1) | 8 (4.5) | 19 (5.2) | 23 (6.2)
Headache | 5 (2.8) | 2 (1.1) | 14 (3.8) | 22 (5.9)

In a 24-week study of initial therapy with JANUVIA in combination with pioglitazone, there were no adverse reactions reported (regardless of investigator assessment of causality) in ≥5% of patients and more commonly than in patients given pioglitazone alone.

No clinically meaningful changes in vital signs or in ECG (including in QTc interval) were observed in patients treated with JANUVIA.

In a pooled analysis of 19 double-blind clinical trials that included data from 10,246 patients randomized to receive sitagliptin 100 mg/day (N=5429) or corresponding (active or placebo) control (N=4817), the incidence of acute pancreatitis was 0.1 per 100 patient-years in each group (4 patients with an event in 4708 patient-years for sitagliptin and 4 patients with an event in 3942 patient-years for control).

Hypoglycemia

In the above studies (N=9), adverse reactions of hypoglycemia were based on all reports of symptomatic hypoglycemia. A concurrent blood glucose measurement was not required although most (74%) reports of hypoglycemia were accompanied by a blood glucose measurement ≤70 mg/dL. When JANUVIA was coadministered with a sulfonylurea or with insulin, the percentage of patients with at least one adverse reaction of hypoglycemia was higher than in the corresponding placebo group (Table 3).

Table 3: Incidence and Rate of Hypoglycemia [Adverse reactions of hypoglycemia were based on all reports of symptomatic hypoglycemia; a concurrent glucose measurement was not required; intent-to-treat population.] in Placebo-Controlled Clinical Studies when JANUVIA was used as Add-On Therapy to Glimepiride (with or without Metformin) or Insulin (with or without Metformin), Regardless of Investigator Assessment of Causality
Add-On to Glimepiride (+/- Metformin) (24 weeks) | JANUVIA 100 mg + Glimepiride (+/- Metformin) | Placebo + Glimepiride (+/- Metformin)
 | N = 222 | N = 219
Overall (%) | 27 (12.2) | 4 (1.8)
Rate (episodes/patient-year) [Based on total number of events (i.e., a single patient may have had multiple events).] | 0.59 | 0.24
Severe (%) [Severe events of hypoglycemia were defined as those events requiring medical assistance or exhibiting depressed level/loss of consciousness or seizure.] | 0 (0.0) | 0 (0.0)
Add-On to Insulin (+/- Metformin) (24 weeks) | JANUVIA 100 mg; + Insulin; (+/- Metformin) | Placebo; + Insulin; (+/- Metformin)
 | N = 322 | N = 319
Overall (%) | 50 (15.5) | 25 (7.8)
Rate (episodes/patient-year) | 1.06 | 0.51
Severe (%) | 2 (0.6) | 1 (0.3)

In a pooled analysis of the two monotherapy studies, the add-on to metformin study, and the add-on to pioglitazone study, the overall incidence of adverse reactions of hypoglycemia was 1.2% in patients treated with JANUVIA 100 mg and 0.9% in patients treated with placebo.

In the study of JANUVIA as add-on combination therapy with metformin and rosiglitazone, the overall incidence of hypoglycemia was 2.2% in patients given add-on JANUVIA and 0.0% in patients given add-on placebo through Week 18. Through Week 54, the overall incidence of hypoglycemia was 3.9% in patients given add-on JANUVIA and 1.0% in patients given add-on placebo.

In the 24-week, placebo-controlled factorial study of initial therapy with JANUVIA in combination with metformin, the incidence of hypoglycemia was 0.6% in patients given placebo, 0.6% in patients given JANUVIA alone, 0.8% in patients given metformin alone, and 1.6% in patients given JANUVIA in combination with metformin.

In the study of JANUVIA as initial therapy with pioglitazone, one patient taking JANUVIA experienced a severe episode of hypoglycemia. There were no severe hypoglycemia episodes reported in other studies except in the study involving coadministration with insulin.

In an additional, 30-week placebo-controlled, study of patients with type 2 diabetes inadequately controlled with metformin comparing the maintenance of sitagliptin 100 mg versus withdrawal of sitagliptin when initiating basal insulin therapy, the event rate and incidence of documented symptomatic hypoglycemia (blood glucose measurement ≤70 mg/dL) did not differ between the sitagliptin and placebo groups.

Laboratory Tests

Across clinical studies, the incidence of laboratory adverse reactions was similar in patients treated with JANUVIA 100 mg compared to patients treated with placebo. A small increase in white blood cell count (WBC) was observed due to an increase in neutrophils. This increase in WBC (of approximately 200 cells/microL vs placebo, in four pooled placebo-controlled clinical studies, with a mean baseline WBC count of approximately 6600 cells/microL) is not considered to be clinically relevant. In a 12-week study of 91 patients with chronic renal insufficiency, 37 patients with moderate renal insufficiency were randomized to JANUVIA 50 mg daily, while 14 patients with the same magnitude of renal impairment were randomized to placebo. Mean (SE) increases in serum creatinine were observed in patients treated with JANUVIA [0.12 mg/dL (0.04)] and in patients treated with placebo [0.07 mg/dL (0.07)]. The clinical significance of this added increase in serum creatinine relative to placebo is not known.

6.2 Postmarketing Experience

Additional adverse reactions have been identified during postapproval use of JANUVIA as monotherapy and/or in combination with other antihyperglycemic agents. Because these reactions are reported voluntarily from a population of uncertain size, it is generally not possible to reliably estimate their frequency or establish a causal relationship to drug exposure.

Hypersensitivity reactions including anaphylaxis, angioedema, rash, urticaria, cutaneous vasculitis, and exfoliative skin conditions including Stevens-Johnson syndrome; hepatic enzyme elevations; acute pancreatitis, including fatal and non-fatal hemorrhagic and necrotizing pancreatitis [see Indications and Usage (1)]; worsening renal function, including acute renal failure (sometimes requiring dialysis), and tubulointerstitial nephritis; severe and disabling arthralgia; bullous pemphigoid; constipation; vomiting; headache; myalgia; pain in extremity; back pain; pruritus; mouth ulceration; stomatitis; rhabdomyolysis.

7 DRUG INTERACTIONS

7.1 Insulin Secretagogues or Insulin

Coadministration of JANUVIA with an insulin secretagogue (e.g., sulfonylurea) or insulin may require lower doses of the insulin secretagogue or insulin to reduce the risk of hypoglycemia. [See Warnings and Precautions (5.4).]

8 USE IN SPECIFIC POPULATIONS

8.1 Pregnancy

Risk Summary

The limited available data with JANUVIA in pregnant women are not sufficient to inform a drug-associated risk for major birth defects and miscarriage. There are risks to the mother and fetus associated with poorly controlled diabetes in pregnancy [see Clinical Considerations]. No adverse developmental effects were observed when sitagliptin was administered to pregnant rats and rabbits during organogenesis at oral doses up to 30-times and 20-times, respectively, the 100 mg clinical dose, based on AUC [see Data].

The estimated background risk of major birth defects is 6-10% in women with pre-gestational diabetes with a Hemoglobin A1c >7% and has been reported to be as high as 20-25% in women with a Hemoglobin A1c >10%. In the U.S. general population, the estimated background risk of major birth defects and miscarriage in clinically recognized pregnancies is 2-4% and 15-20%, respectively.

Clinical Considerations

Disease-Associated Maternal and/or Embryo/Fetal Risk

Poorly controlled diabetes in pregnancy increases the maternal risk for diabetic ketoacidosis, pre-eclampsia, spontaneous abortions, preterm delivery, and delivery complications. Poorly controlled diabetes increases the fetal risk for major birth defects, still birth, and macrosomia related morbidity.

Data

Animal Data

In embryo-fetal development studies, sitagliptin administered to pregnant rats and rabbits during organogenesis (gestation day 6 to 20) did not adversely affect developmental outcomes at oral doses up to 250 mg/kg (30-times the 100 mg clinical dose) and 125 mg/kg (20-times the 100 mg clinical dose), respectively, based on AUC. Higher doses in rats associated with maternal toxicity increased the incidence of rib malformations in offspring at 1000 mg/kg, or approximately 100-times the clinical dose, based on AUC. Placental transfer of sitagliptin was observed in pregnant rats and rabbits.

Sitagliptin administered to female rats from gestation day 6 to lactation day 21 caused no functional or behavioral toxicity in offspring of rats at doses up to 1000 mg/kg.

8.2 Lactation

Risk Summary

There is no information regarding the presence of JANUVIA in human milk, the effects on the breastfed infant, or the effects on milk production. Sitagliptin is present in rat milk and therefore possibly present in human milk [see Data]. The developmental and health benefits of breastfeeding should be considered along with the mother's clinical need for JANUVIA and any potential adverse effects on the breastfed infant from JANUVIA or from the underlying maternal condition.

Data

Sitagliptin is secreted in the milk of lactating rats at a milk to plasma ratio of 4:1.

8.4 Pediatric Use

The safety and effectiveness of JANUVIA have not been established in pediatric patients.

Three 20-week double-blind, placebo-controlled studies each with 34-week extensions were conducted to evaluate the efficacy and safety of sitagliptin in 410 pediatric patients aged 10 to 17 years with inadequately controlled type 2 diabetes, with or without insulin therapy (HbA1c 6.5-10% for patients not on insulin, HbA1c 7-10% for patients on insulin). At study entry, patients in study 1 were not treated with oral antihyperglycemic agents; patients in studies 2 and 3 were on maximally tolerated metformin therapy. The primary efficacy endpoint was the change from baseline in HbA1c after 20 weeks of therapy. The pre-specified primary efficacy analyses included data from study 1 and pooled data from studies 2 and 3, regardless of glycemic rescue or treatment discontinuation.

In both efficacy analyses, the effect of treatment with sitagliptin was not significantly different from placebo. In study 1, the mean baseline HbA1c was 7.5%, and 12% of patients were on insulin therapy. At week 20, the change from baseline in HbA1c in patients treated with JANUVIA (N=95) was 0.06% compared to 0.23% in patients treated with placebo (N=95), a difference of -0.17% (95% CI: -0.62, 0.28). In studies 2 and 3, the mean baseline HbA1c was 8.0%, 15% of patients were on insulin and 72% were on metformin HCl doses of greater than 1,500 mg daily. At week 20, the change from baseline in HbA1c in patients treated with sitagliptin (N=107) was -0.23% compared to 0.09% in patients treated with placebo (N=113), a difference of -0.33% (95% CI: -0.70, 0.05).

8.5 Geriatric Use

Of the total number of subjects (N=3884) in pre-approval clinical safety and efficacy studies of JANUVIA, 725 patients were 65 years and over, while 61 patients were 75 years and over. No overall differences in safety or effectiveness were observed between subjects 65 years and over and younger subjects. While this and other reported clinical experience have not identified differences in responses between the elderly and younger patients, greater sensitivity of some older individuals cannot be ruled out.

Because sitagliptin is substantially excreted by the kidney, and because aging can be associated with reduced renal function, renal function should be assessed more frequently in elderly patients [see Dosage and Administration (2.2), Warnings and Precautions (5.3)].

8.6 Renal Impairment

Sitagliptin is excreted by the kidney, and sitagliptin exposure is increased in patients with renal impairment. Lower dosages are recommended in patients with eGFR less than 45 mL/min/1.73 m^2 (moderate and severe renal impairment, as well as in ESRD patients requiring dialysis). [See Dosage and Administration (2.2); Clinical Pharmacology (12.3).]

10 OVERDOSAGE

In the event of an overdose with JANUVIA, contact the Poison Control Center.

In the event of an overdose, it is reasonable to employ supportive measures, e.g., remove unabsorbed material from the gastrointestinal tract, employ clinical monitoring (including obtaining an electrocardiogram), and institute supportive therapy as dictated by the patient's clinical status.

Sitagliptin is modestly dialyzable. In clinical studies, approximately 13.5% of the dose was removed over a 3- to 4-hour hemodialysis session. Prolonged hemodialysis may be considered if clinically appropriate. It is not known if sitagliptin is dialyzable by peritoneal dialysis.

11 DESCRIPTION

JANUVIA Tablets contain sitagliptin phosphate, an orally-active inhibitor of the dipeptidyl peptidase-4 (DPP-4) enzyme.

Sitagliptin phosphate monohydrate is described chemically as 7-[(3R)-3-amino-1-oxo-4-(2,4,5-trifluorophenyl)butyl]-5,6,7,8-tetrahydro-3-(trifluoromethyl)-1,2,4-triazolo[4,3-a]pyrazine phosphate (1:1) monohydrate.

The empirical formula is C16H15F6N5O•H3PO4•H2O and the molecular weight is 523.32. The structural formula is:

Sitagliptin phosphate monohydrate is a white to off-white, crystalline, non-hygroscopic powder. It is soluble in water and N,N-dimethyl formamide; slightly soluble in methanol; very slightly soluble in ethanol, acetone, and acetonitrile; and insoluble in isopropanol and isopropyl acetate.

Each film-coated tablet of JANUVIA contains 32.13, 64.25, or 128.5 mg of sitagliptin phosphate monohydrate, which is equivalent to 25, 50, or 100 mg, respectively, of free base and the following inactive ingredients: microcrystalline cellulose, anhydrous dibasic calcium phosphate, croscarmellose sodium, magnesium stearate, sodium stearyl fumarate, and propyl gallate. In addition, the film coating contains the following inactive ingredients: polyvinyl alcohol, polyethylene glycol, talc, titanium dioxide, red iron oxide, and yellow iron oxide.

12 CLINICAL PHARMACOLOGY

12.1 Mechanism of Action

Sitagliptin is a DPP-4 inhibitor, which is believed to exert its actions in patients with type 2 diabetes mellitus by slowing the inactivation of incretin hormones. Concentrations of the active intact hormones are increased by sitagliptin, thereby increasing and prolonging the action of these hormones. Incretin hormones, including glucagon-like peptide-1 (GLP-1) and glucose-dependent insulinotropic polypeptide (GIP), are released by the intestine throughout the day, and levels are increased in response to a meal. These hormones are rapidly inactivated by the enzyme, DPP-4. The incretins are part of an endogenous system involved in the physiologic regulation of glucose homeostasis. When blood glucose concentrations are normal or elevated, GLP-1 and GIP increase insulin synthesis and release from pancreatic beta cells by intracellular signaling pathways involving cyclic AMP. GLP-1 also lowers glucagon secretion from pancreatic alpha cells, leading to reduced hepatic glucose production. By increasing and prolonging active incretin levels, sitagliptin increases insulin release and decreases glucagon levels in the circulation in a glucose-dependent manner. Sitagliptin demonstrates selectivity for DPP-4 and does not inhibit DPP-8 or DPP-9 activity in vitro at concentrations approximating those from therapeutic doses.

12.2 Pharmacodynamics

General

In patients with type 2 diabetes mellitus, administration of sitagliptin led to inhibition of DPP-4 enzyme activity for a 24-hour period. After an oral glucose load or a meal, this DPP-4 inhibition resulted in a 2- to 3-fold increase in circulating levels of active GLP-1 and GIP, decreased glucagon concentrations, and increased responsiveness of insulin release to glucose, resulting in higher C-peptide and insulin concentrations. The rise in insulin with the decrease in glucagon was associated with lower fasting glucose concentrations and reduced glucose excursion following an oral glucose load or a meal.

In studies with healthy subjects, sitagliptin did not lower blood glucose or cause hypoglycemia.

Sitagliptin and Metformin hydrochloride Coadministration

In a two-day study in healthy subjects, sitagliptin alone increased active GLP-1 concentrations, whereas metformin alone increased active and total GLP-1 concentrations to similar extents. Coadministration of sitagliptin and metformin had an additive effect on active GLP-1 concentrations. Sitagliptin, but not metformin, increased active GIP concentrations. It is unclear how these findings relate to changes in glycemic control in patients with type 2 diabetes mellitus.

Cardiac Electrophysiology

In a randomized, placebo-controlled crossover study, 79 healthy subjects were administered a single oral dose of sitagliptin 100 mg, sitagliptin 800 mg (8 times the recommended dose), and placebo. At the recommended dose of 100 mg, there was no effect on the QTc interval obtained at the peak plasma concentration, or at any other time during the study. Following the 800 mg dose, the maximum increase in the placebo-corrected mean change in QTc from baseline was observed at 3 hours postdose and was 8.0 msec. This increase is not considered to be clinically significant. At the 800 mg dose, peak sitagliptin plasma concentrations were approximately 11 times higher than the peak concentrations following a 100-mg dose.

In patients with type 2 diabetes mellitus administered sitagliptin 100 mg (N=81) or sitagliptin 200 mg (N=63) daily, there were no meaningful changes in QTc interval based on ECG data obtained at the time of expected peak plasma concentration.

12.3 Pharmacokinetics

The pharmacokinetics of sitagliptin have been extensively characterized in healthy subjects and patients with type 2 diabetes mellitus. Following a single oral 100-mg dose to healthy volunteers, mean plasma AUC of sitagliptin was 8.52 μM•hr, Cmax was 950 nM, and apparent terminal half-life (t1/2) was 12.4 hours. Plasma AUC of sitagliptin increased in a dose-proportional manner and increased approximately 14% following 100 mg doses at steady-state compared to the first dose. The intra-subject and inter-subject coefficients of variation for sitagliptin AUC were small (5.8% and 15.1%). The pharmacokinetics of sitagliptin was generally similar in healthy subjects and in patients with type 2 diabetes mellitus.

Absorption

After oral administration of a 100 mg dose to healthy subjects, sitagliptin was rapidly absorbed with peak plasma concentrations (median Tmax) occurring 1 to 4 hours postdose. The absolute bioavailability of sitagliptin is approximately 87%.

Effect of Food

Coadministration of a high-fat meal with sitagliptin had no effect on the pharmacokinetics of sitagliptin.

Distribution

The mean volume of distribution at steady state following a single 100-mg intravenous dose of sitagliptin to healthy subjects is approximately 198 liters. The fraction of sitagliptin reversibly bound to plasma proteins is low (38%).

Elimination

Approximately 79% of sitagliptin is excreted unchanged in the urine with metabolism being a minor pathway of elimination. The apparent terminal t1/2 following a 100 mg oral dose of sitagliptin was approximately 12.4 hours and renal clearance was approximately 350 mL/min.

Metabolism

Following a [^14C]sitagliptin oral dose, approximately 16% of the radioactivity was excreted as metabolites of sitagliptin. Six metabolites were detected at trace levels and are not expected to contribute to the plasma DPP-4 inhibitory activity of sitagliptin. In vitro studies indicated that the primary enzyme responsible for the limited metabolism of sitagliptin was CYP3A4, with contribution from CYP2C8.

Excretion

Following administration of an oral [^14C]sitagliptin dose to healthy subjects, approximately 100% of the administered radioactivity was eliminated in feces (13%) or urine (87%) within one week of dosing.

Elimination of sitagliptin occurs primarily via renal excretion and involves active tubular secretion. Sitagliptin is a substrate for human organic anion transporter-3 (hOAT-3), which may be involved in the renal elimination of sitagliptin. The clinical relevance of hOAT-3 in sitagliptin transport has not been established. Sitagliptin is also a substrate of P-glycoprotein (P-gp), which may also be involved in mediating the renal elimination of sitagliptin. However, cyclosporine, a P-gp inhibitor, did not reduce the renal clearance of sitagliptin.

Specific Populations

Patients with Renal Impairment

An approximately 2-fold increase in the plasma AUC of sitagliptin was observed in patients with moderate renal impairment with eGFR of 30 to less than 45 mL/min/1.73 m^2, and an approximately 4-fold increase was observed in patients with severe renal impairment, including patients with ESRD on hemodialysis, as compared to normal healthy control subjects.

Patients with Hepatic Impairment

In patients with moderate hepatic impairment (Child-Pugh score 7 to 9), mean AUC and Cmax of sitagliptin increased approximately 21% and 13%, respectively, compared to healthy matched controls following administration of a single 100-mg dose of sitagliptin. These differences are not considered to be clinically meaningful.

There is no clinical experience in patients with severe hepatic impairment (Child-Pugh score >9).

Effects of Age, Body Mass Index (BMI), Gender, and Race

Based on a population pharmacokinetic analysis or a composite analysis of available pharmacokinetic data, BMI, gender, and race do not have a clinically meaningful effect on the pharmacokinetics of sitagliptin. When the effects of age on renal function are taken into account, age alone did not have a clinically meaningful impact on the pharmacokinetics of sitagliptin based on a population pharmacokinetic analysis. Elderly subjects (65 to 80 years) had approximately 19% higher plasma concentrations of sitagliptin compared to younger subjects.

Drug Interaction Studies

In Vitro Assessment of Drug Interactions

Sitagliptin is not an inhibitor of CYP isozymes CYP3A4, 2C8, 2C9, 2D6, 1A2, 2C19 or 2B6, and is not an inducer of CYP3A4. Sitagliptin is a P-gp substrate, but does not inhibit P-gp mediated transport of digoxin. Based on these results, sitagliptin is considered unlikely to cause interactions with other drugs that utilize these pathways.

Sitagliptin is not extensively bound to plasma proteins. Therefore, the propensity of sitagliptin to be involved in clinically meaningful drug-drug interactions mediated by plasma protein binding displacement is very low.

In Vivo Assessment of Drug Interactions

Effects of Sitagliptin on Other Drugs

In clinical studies, sitagliptin did not meaningfully alter the pharmacokinetics of metformin, glyburide, simvastatin, rosiglitazone, digoxin, warfarin, or an oral contraceptive (ethinyl estradiol and norethindrone) (Table 4), providing in vivo evidence of a low propensity for causing drug interactions with substrates of CYP3A4, CYP2C8, CYP2C9, P-gp, and organic cationic transporter (OCT).

Table 4: Effect of Sitagliptin on Systemic Exposure of Coadministered Drugs
Coadministered Drug | Dose of Coadministered Drug [All doses administered as single dose unless otherwise specified.] | Dose of Sitagliptin | Geometric Mean Ratio (ratio with/without sitagliptin) No Effect = 1.00
Coadministered Drug | Dose of Coadministered Drug [All doses administered as single dose unless otherwise specified.] | Dose of Sitagliptin |  | AUC [AUC is reported as AUC0-∞ unless otherwise specified.] | Cmax
Digoxin | 0.25 mg [Multiple dose.] once daily for 10 days | 100 mg once daily for 10 days | Digoxin | 1.11 [AUC0-24hr.] | 1.18
Glyburide | 1.25 mg | 200 mg once daily for 6 days | Glyburide | 1.09 | 1.01
Simvastatin | 20 mg | 200 mg once daily for 5 days | Simvastatin | 0.85 [AUC0-last.] | 0.80
Simvastatin | 20 mg | 200 mg once daily for 5 days | Simvastatin Acid | 1.12 | 1.06
Rosiglitazone | 4 mg | 200 mg once daily for 5 days | Rosiglitazone | 0.98 | 0.99
Warfarin | 30 mg single dose on day 5 | 200 mg once daily for 11 days | S(-) Warfarin | 0.95 | 0.89
Warfarin | 30 mg single dose on day 5 | 200 mg once daily for 11 days | R(+) Warfarin | 0.99 | 0.89
Ethinyl estradiol and norethindrone | 21 days once daily of 35 µg ethinyl estradiol with norethindrone 0.5 mg × 7 days, 0.75 mg × 7 days, 1.0 mg × 7 days | 200 mg once daily for 21 days | Ethinyl estradiol | 0.99 | 0.97
Ethinyl estradiol and norethindrone | 21 days once daily of 35 µg ethinyl estradiol with norethindrone 0.5 mg × 7 days, 0.75 mg × 7 days, 1.0 mg × 7 days | 200 mg once daily for 21 days | Norethindrone | 1.03 | 0.98
Metformin HCl | 1000 mg twice daily for 14 days | 50 mg twice daily for 7 days | Metformin | 1.02 [AUC0-12hr.] | 0.97

Effects of Other Drugs on Sitagliptin

Clinical data described below suggest that sitagliptin is not susceptible to clinically meaningful interactions by coadministered medications (Table 5).

Table 5: Effect of Coadministered Drugs on Systemic Exposure of Sitagliptin
Coadministered Drug | Dose of Coadministered Drug [All doses administered as single dose unless otherwise specified.] | Dose of Sitagliptin | Geometric Mean Ratio (ratio with/without coadministered drug) No Effect = 1.00
Coadministered Drug | Dose of Coadministered Drug [All doses administered as single dose unless otherwise specified.] | Dose of Sitagliptin |  | AUC [AUC is reported as AUC0-∞ unless otherwise specified.] | Cmax
Cyclosporine | 600 mg once daily | 100 mg once daily | Sitagliptin | 1.29 | 1.68
Metformin HCl | 1000 mg [Multiple dose.] twice daily for 14 days | 50 mg twice daily for 7 days | Sitagliptin | 1.02 [AUC0-12hr.] | 1.05

13 NONCLINICAL TOXICOLOGY

13.1 Carcinogenesis, Mutagenesis, Impairment of Fertility

A two-year carcinogenicity study was conducted in male and female rats given oral doses of sitagliptin of 50, 150, and 500 mg/kg/day. There was an increased incidence of combined liver adenoma/carcinoma in males and females and of liver carcinoma in females at 500 mg/kg. This dose results in exposures approximately 60 times the human exposure at the maximum recommended daily adult human dose (MRHD) of 100 mg/day based on AUC comparisons. Liver tumors were not observed at 150 mg/kg, approximately 20 times the human exposure at the MRHD. A two-year carcinogenicity study was conducted in male and female mice given oral doses of sitagliptin of 50, 125, 250, and 500 mg/kg/day. There was no increase in the incidence of tumors in any organ up to 500 mg/kg, approximately 70 times human exposure at the MRHD. Sitagliptin was not mutagenic or clastogenic with or without metabolic activation in the Ames bacterial mutagenicity assay, a Chinese hamster ovary (CHO) chromosome aberration assay, an in vitro cytogenetics assay in CHO, an in vitro rat hepatocyte DNA alkaline elution assay, and an in vivo micronucleus assay.

In rat fertility studies with oral gavage doses of 125, 250, and 1000 mg/kg, males were treated for 4 weeks prior to mating, during mating, up to scheduled termination (approximately 8 weeks total) and females were treated 2 weeks prior to mating through gestation day 7. No adverse effect on fertility was observed at 125 mg/kg (approximately 12 times human exposure at the MRHD of 100 mg/day based on AUC comparisons). At higher doses, nondose-related increased resorptions in females were observed (approximately 25 and 100 times human exposure at the MRHD based on AUC comparison).

14 CLINICAL STUDIES

There were approximately 5200 patients with type 2 diabetes randomized in nine double-blind, placebo-controlled clinical safety and efficacy studies conducted to evaluate the effects of sitagliptin on glycemic control. In a pooled analysis of seven of these studies, the ethnic/racial distribution was approximately 59% white, 20% Hispanic, 10% Asian, 6% black, and 6% other groups. Patients had an overall mean age of approximately 55 years (range 18 to 87 years). In addition, an active (glipizide)-controlled study of 52-weeks duration was conducted in 1172 patients with type 2 diabetes who had inadequate glycemic control on metformin.

In patients with type 2 diabetes, treatment with JANUVIA produced clinically significant improvements in hemoglobin A1C, fasting plasma glucose (FPG) and 2-hour post-prandial glucose (PPG) compared to placebo.

14.1 Monotherapy

A total of 1262 patients with type 2 diabetes participated in two double-blind, placebo-controlled studies, one of 18-week and another of 24-week duration, to evaluate the efficacy and safety of JANUVIA monotherapy. In both monotherapy studies, patients currently on an antihyperglycemic agent discontinued the agent, and underwent a diet, exercise, and drug washout period of about 7 weeks. Patients with inadequate glycemic control (A1C 7% to 10%) after the washout period were randomized after completing a 2-week single-blind placebo run-in period; patients not currently on antihyperglycemic agents (off therapy for at least 8 weeks) with inadequate glycemic control (A1C 7% to 10%) were randomized after completing the 2-week single-blind placebo run-in period. In the 18-week study, 521 patients were randomized to placebo, JANUVIA 100 mg, or JANUVIA 200 mg, and in the 24-week study 741 patients were randomized to placebo, JANUVIA 100 mg, or JANUVIA 200 mg. Patients who failed to meet specific glycemic goals during the studies were treated with metformin rescue, added on to placebo or JANUVIA.

Treatment with JANUVIA at 100 mg daily provided significant improvements in A1C, FPG, and 2-hour PPG compared to placebo (Table 6). In the 18-week study, 9% of patients receiving JANUVIA 100 mg and 17% who received placebo required rescue therapy. In the 24-week study, 9% of patients receiving JANUVIA 100 mg and 21% of patients receiving placebo required rescue therapy. The improvement in A1C compared to placebo was not affected by gender, age, race, prior antihyperglycemic therapy, or baseline BMI. As is typical for trials of agents to treat type 2 diabetes, the mean reduction in A1C with JANUVIA appears to be related to the degree of A1C elevation at baseline. In these 18- and 24-week studies, among patients who were not on an antihyperglycemic agent at study entry, the reductions from baseline in A1C were -0.7% and -0.8%, respectively, for those given JANUVIA, and -0.1% and -0.2%, respectively, for those given placebo. Overall, the 200 mg daily dose did not provide greater glycemic efficacy than the 100 mg daily dose. The effect of JANUVIA on lipid endpoints was similar to placebo. Body weight did not increase from baseline with JANUVIA therapy in either study, compared to a small reduction in patients given placebo.

Table 6: Glycemic Parameters in 18- and 24-Week Placebo-Controlled Studies of JANUVIA in Patients with Type 2 Diabetes [Intent-to-treat population using last observation on study prior to metformin rescue therapy.]
 | 18-Week Study |  | 24-Week Study
 | JANUVIA 100 mg | Placebo | JANUVIA 100 mg | Placebo
A1C (%) | N = 193 | N = 103 | N = 229 | N = 244
Baseline (mean) | 8.0 | 8.1 | 8.0 | 8.0
Change from baseline (adjusted mean [Least squares means adjusted for prior antihyperglycemic therapy status and baseline value.]) | -0.5 | 0.1 | -0.6 | 0.2
Difference from placebo (adjusted mean) (95% CI) | -0.6 [p<0.001 compared to placebo.] (-0.8, -0.4) |  | -0.8 (-1.0, -0.6)
Patients (%) achieving A1C <7% | 69 (36%) | 16 (16%) | 93 (41%) | 41 (17%)
FPG (mg/dL) | N = 201 | N = 107 | N = 234 | N = 247
Baseline (mean) | 180 | 184 | 170 | 176
Change from baseline (adjusted mean) | -13 | 7 | -12 | 5
Difference from placebo (adjusted mean) (95% CI) | -20 (-31, -9) |  | -17 (-24, -10)
2-hour PPG (mg/dL) | [Data not available.] |  | N = 201 | N = 204
Baseline (mean) |  |  | 257 | 271
Change from baseline (adjusted mean) |  |  | -49 | -2
Difference from placebo (adjusted mean) (95% CI) |  |  | -47 (-59, -34)

Additional Monotherapy Study

A multinational, randomized, double-blind, placebo-controlled study was also conducted to assess the safety and tolerability of JANUVIA in 91 patients with type 2 diabetes and chronic renal insufficiency (creatinine clearance <50 mL/min). Patients with moderate renal insufficiency received 50 mg daily of JANUVIA and those with severe renal insufficiency or with ESRD on hemodialysis or peritoneal dialysis received 25 mg daily. In this study, the safety and tolerability of JANUVIA were generally similar to placebo. A small increase in serum creatinine was reported in patients with moderate renal insufficiency treated with JANUVIA relative to those on placebo. In addition, the reductions in A1C and FPG with JANUVIA compared to placebo were generally similar to those observed in other monotherapy studies. [See Clinical Pharmacology (12.3).]

14.2 Combination Therapy

Add-on Combination Therapy with Metformin

A total of 701 patients with type 2 diabetes participated in a 24-week, randomized, double-blind, placebo-controlled study designed to assess the efficacy of JANUVIA in combination with metformin. Patients already on metformin HCl (N=431) at a dose of at least 1500 mg per day were randomized after completing a 2-week single-blind placebo run-in period. Patients on metformin and another antihyperglycemic agent (N=229) and patients not on any antihyperglycemic agents (off therapy for at least 8 weeks, N=41) were randomized after a run-in period of approximately 10 weeks on metformin HCl (at a dose of at least 1500 mg per day) in monotherapy. Patients with inadequate glycemic control (A1C 7% to 10%) were randomized to the addition of either 100 mg of JANUVIA or placebo, administered once daily. Patients who failed to meet specific glycemic goals during the studies were treated with pioglitazone rescue.

In combination with metformin, JANUVIA provided significant improvements in A1C, FPG, and 2-hour PPG compared to placebo with metformin (Table 7). Rescue glycemic therapy was used in 5% of patients treated with JANUVIA 100 mg and 14% of patients treated with placebo. A similar decrease in body weight was observed for both treatment groups.

Table 7: Glycemic Parameters at Final Visit (24-Week Study) for JANUVIA in Add-on Combination Therapy with Metformin [Intent-to-treat population using last observation on study prior to pioglitazone rescue therapy.]
 | JANUVIA 100 mg + Metformin | Placebo + Metformin
A1C (%) | N = 453 | N = 224
Baseline (mean) | 8.0 | 8.0
Change from baseline (adjusted mean [Least squares means adjusted for prior antihyperglycemic therapy and baseline value.]) | -0.7 | -0.0
Difference from placebo + metformin (adjusted mean) (95% CI) | -0.7 [p<0.001 compared to placebo + metformin.] (-0.8, -0.5)
Patients (%) achieving A1C <7% | 213 (47%) | 41 (18%)
FPG (mg/dL) | N = 454 | N = 226
Baseline (mean) | 170 | 174
Change from baseline (adjusted mean) | -17 | 9
Difference from placebo + metformin (adjusted mean) (95% CI) | -25 (-31, -20)
2-hour PPG (mg/dL) | N = 387 | N = 182
Baseline (mean) | 275 | 272
Change from baseline (adjusted mean) | -62 | -11
Difference from placebo + metformin (adjusted mean) (95% CI) | -51 (-61, -41)

Initial Combination Therapy with Metformin

A total of 1091 patients with type 2 diabetes and inadequate glycemic control on diet and exercise participated in a 24-week, randomized, double-blind, placebo-controlled factorial study designed to assess the efficacy of sitagliptin as initial therapy in combination with metformin. Patients on an antihyperglycemic agent (N=541) discontinued the agent, and underwent a diet, exercise, and drug washout period of up to 12 weeks duration. After the washout period, patients with inadequate glycemic control (A1C 7.5% to 11%) were randomized after completing a 2-week single-blind placebo run-in period. Patients not on antihyperglycemic agents at study entry (N=550) with inadequate glycemic control (A1C 7.5% to 11%) immediately entered the 2-week single-blind placebo run-in period and then were randomized. Approximately equal numbers of patients were randomized to receive initial therapy with placebo, 100 mg of JANUVIA once daily, 500 mg or 1000 mg of metformin HCl twice daily, or 50 mg of sitagliptin twice daily in combination with 500 mg or 1000 mg of metformin HCl twice daily. Patients who failed to meet specific glycemic goals during the study were treated with glyburide (glibenclamide) rescue.

Initial therapy with the combination of JANUVIA and metformin provided significant improvements in A1C, FPG, and 2-hour PPG compared to placebo, to metformin alone, and to JANUVIA alone (Table 8, Figure 1). Mean reductions from baseline in A1C were generally greater for patients with higher baseline A1C values. For patients not on an antihyperglycemic agent at study entry, mean reductions from baseline in A1C were: JANUVIA 100 mg once daily, -1.1%; metformin HCl 500 mg bid, -1.1%; metformin HCl 1000 mg bid, -1.2%; sitagliptin 50 mg bid with metformin HCl 500 mg bid, -1.6%; sitagliptin 50 mg bid with metformin HCl 1000 mg bid, -1.9%; and for patients receiving placebo, -0.2%. Lipid effects were generally neutral. The decrease in body weight in the groups given sitagliptin in combination with metformin was similar to that in the groups given metformin alone or placebo.

Table 8: Glycemic Parameters at Final Visit (24-Week Study) for Sitagliptin and Metformin, Alone and in Combination as Initial Therapy [Intent-to-treat population using last observation on study prior to glyburide (glibenclamide) rescue therapy.]
 | Placebo | Sitagliptin (JANUVIA) 100 mg QD | Metformin HCl 500 mg bid | Metformin HCl 1000 mg bid | Sitagliptin 50 mg bid + Metformin HCl 500 mg bid | Sitagliptin 50 mg bid + Metformin HCl 1000 mg bid
A1C (%) | N = 165 | N = 175 | N = 178 | N = 177 | N = 183 | N = 178
Baseline (mean) | 8.7 | 8.9 | 8.9 | 8.7 | 8.8 | 8.8
Change from baseline (adjusted mean [Least squares means adjusted for prior antihyperglycemic therapy status and baseline value.]) | 0.2 | -0.7 | -0.8 | -1.1 | -1.4 | -1.9
Difference from placebo (adjusted mean) (95% CI) |  | -0.8 [p<0.001 compared to placebo.] (-1.1, -0.6) | -1.0 (-1.2, -0.8) | -1.3 (-1.5, -1.1) | -1.6 (-1.8, -1.3) | -2.1 (-2.3, -1.8)
Patients (%) achieving A1C <7% | 15 (9%) | 35 (20%) | 41 (23%) | 68 (38%) | 79 (43%) | 118 (66%)
% Patients receiving rescue medication | 32 | 21 | 17 | 12 | 8 | 2
FPG (mg/dL) | N = 169 | N = 178 | N = 179 | N = 179 | N = 183 | N = 180
Baseline (mean) | 196 | 201 | 205 | 197 | 204 | 197
Change from baseline (adjusted mean) | 6 | -17 | -27 | -29 | -47 | -64
Difference from placebo (adjusted mean) (95% CI) |  | -23 (-33, -14) | -33 (-43, -24) | -35 (-45, -26) | -53 (-62, -43) | -70 (-79, -60)
2-hour PPG (mg/dL) | N = 129 | N = 136 | N = 141 | N = 138 | N = 147 | N = 152
Baseline (mean) | 277 | 285 | 293 | 283 | 292 | 287
Change from baseline (adjusted mean) | 0 | -52 | -53 | -78 | -93 | -117
Difference from placebo (adjusted mean) (95% CI) |  | -52 (-67, -37) | -54 (-69, -39) | -78 (-93, -63) | -93 (-107, -78) | -117 (-131, -102)

Figure 1: Mean Change from Baseline for A1C (%) over 24 Weeks with Sitagliptin and Metformin, Alone and in Combination as Initial Therapy in Patients with Type 2 Diabetes [All Patients Treated Population: least squares means adjusted for prior antihyperglycemic therapy and baseline value.]

Initial combination therapy or maintenance of combination therapy may not be appropriate for all patients. These management options are left to the discretion of the health care provider.

Active-Controlled Study vs Glipizide in Combination with Metformin

The efficacy of JANUVIA was evaluated in a 52-week, double-blind, glipizide-controlled noninferiority trial in patients with type 2 diabetes. Patients not on treatment or on other antihyperglycemic agents entered a run-in treatment period of up to 12 weeks duration with metformin HCl monotherapy (dose of ≥1500 mg per day) which included washout of medications other than metformin, if applicable. After the run-in period, those with inadequate glycemic control (A1C 6.5% to 10%) were randomized 1:1 to the addition of JANUVIA 100 mg once daily or glipizide for 52 weeks. Patients receiving glipizide were given an initial dosage of 5 mg/day and then electively titrated over the next 18 weeks to a maximum dosage of 20 mg/day as needed to optimize glycemic control. Thereafter, the glipizide dose was to be kept constant, except for down-titration to prevent hypoglycemia. The mean dose of glipizide after the titration period was 10 mg.

After 52 weeks, JANUVIA and glipizide had similar mean reductions from baseline in A1C in the intent-to-treat analysis (Table 9). These results were consistent with the per protocol analysis (Figure 2). A conclusion in favor of the non-inferiority of JANUVIA to glipizide may be limited to patients with baseline A1C comparable to those included in the study (over 70% of patients had baseline A1C <8% and over 90% had A1C <9%).

Table 9: Glycemic Parameters in a 52-Week Study Comparing JANUVIA to Glipizide as Add-On Therapy in Patients Inadequately Controlled on Metformin (Intent-to-Treat Population) [The intent-to-treat analysis used the patients' last observation in the study prior to discontinuation.]
 | JANUVIA 100 mg | Glipizide
A1C (%) | N = 576 | N = 559
Baseline (mean) | 7.7 | 7.6
Change from baseline (adjusted mean [Least squares means adjusted for prior antihyperglycemic therapy status and baseline A1C value.]) | -0.5 | -0.6
FPG (mg/dL) | N = 583 | N = 568
Baseline (mean) | 166 | 164
Change from baseline (adjusted mean) | -8 | -8

Figure 2: Mean Change from Baseline for A1C (%) Over 52 Weeks in a Study Comparing JANUVIA to Glipizide as Add-On Therapy in Patients Inadequately Controlled on Metformin (Per Protocol Population) [The per protocol population (mean baseline A1C of 7.5%) included patients without major protocol violations who had observations at baseline and at Week 52.]

The incidence of hypoglycemia in the JANUVIA group (4.9%) was significantly (p<0.001) lower than that in the glipizide group (32.0%). Patients treated with JANUVIA exhibited a significant mean decrease from baseline in body weight compared to a significant weight gain in patients administered glipizide (-1.5 kg vs +1.1 kg).

Add-on Combination Therapy with Pioglitazone

A total of 353 patients with type 2 diabetes participated in a 24-week, randomized, double-blind, placebo-controlled study designed to assess the efficacy of JANUVIA in combination with pioglitazone. Patients on any oral antihyperglycemic agent in monotherapy (N=212) or on a PPARγ agent in combination therapy (N=106) or not on an antihyperglycemic agent (off therapy for at least 8 weeks, N=34) were switched to monotherapy with pioglitazone (at a dose of 30-45 mg per day), and completed a run-in period of approximately 12 weeks in duration. After the run-in period on pioglitazone monotherapy, patients with inadequate glycemic control (A1C 7% to 10%) were randomized to the addition of either 100 mg of JANUVIA or placebo, administered once daily. Patients who failed to meet specific glycemic goals during the studies were treated with metformin rescue. Glycemic endpoints measured were A1C and fasting glucose.

In combination with pioglitazone, JANUVIA provided significant improvements in A1C and FPG compared to placebo with pioglitazone (Table 10). Rescue therapy was used in 7% of patients treated with JANUVIA 100 mg and 14% of patients treated with placebo. There was no significant difference between JANUVIA and placebo in body weight change.

Table 10: Glycemic Parameters at Final Visit (24-Week Study) for JANUVIA in Add-on Combination Therapy with Pioglitazone [Intent-to-treat population using last observation on study prior to metformin rescue therapy.]
 | JANUVIA 100 mg + Pioglitazone | Placebo + Pioglitazone
A1C (%) | N = 163 | N = 174
Baseline (mean) | 8.1 | 8.0
Change from baseline (adjusted mean [Least squares means adjusted for prior antihyperglycemic therapy status and baseline value.]) | -0.9 | -0.2
Difference from placebo + pioglitazone (adjusted mean) (95% CI) | -0.7 [p<0.001 compared to placebo + pioglitazone.] (-0.9, -0.5)
Patients (%) achieving A1C <7% | 74 (45%) | 40 (23%)
FPG (mg/dL) | N = 163 | N = 174
Baseline (mean) | 168 | 166
Change from baseline (adjusted mean) | -17 | 1
Difference from placebo + pioglitazone (adjusted mean) (95% CI) | -18 (-24, -11)

Initial Combination Therapy with Pioglitazone

A total of 520 patients with type 2 diabetes and inadequate glycemic control on diet and exercise participated in a 24-week, randomized, double-blind study designed to assess the efficacy of JANUVIA as initial therapy in combination with pioglitazone. Patients not on antihyperglycemic agents at study entry (<4 weeks cumulative therapy over the past 2 years, and with no treatment over the prior 4 months) with inadequate glycemic control (A1C 8% to 12%) immediately entered the 2-week single-blind placebo run-in period and then were randomized. Approximately equal numbers of patients were randomized to receive initial therapy with 100 mg of JANUVIA in combination with 30 mg of pioglitazone once daily or 30 mg of pioglitazone once daily as monotherapy. There was no glycemic rescue therapy in this study.

Initial therapy with the combination of JANUVIA and pioglitazone provided significant improvements in A1C, FPG, and 2-hour PPG compared to pioglitazone monotherapy (Table 11). The improvement in A1C was generally consistent across subgroups defined by gender, age, race, baseline BMI, baseline A1C, or duration of disease. In this study, patients treated with JANUVIA in combination with pioglitazone had a mean increase in body weight of 1.1 kg compared to pioglitazone alone (3.0 kg vs. 1.9 kg). Lipid effects were generally neutral.

Table 11: Glycemic Parameters at Final Visit (24-Week Study) for JANUVIA in Combination with Pioglitazone as Initial Therapy [Intent-to-treat population using last observation on study.]
 | JANUVIA 100 mg + Pioglitazone | Pioglitazone
A1C (%) | N = 251 | N = 246
Baseline (mean) | 9.5 | 9.4
Change from baseline (adjusted mean [Least squares means adjusted for baseline value.]) | -2.4 | -1.5
Difference from pioglitazone (adjusted mean) (95% CI) | -0.9 [p<0.001 compared to placebo + pioglitazone.] (-1.1, -0.7)
Patients (%) achieving A1C <7% | 151 (60%) | 68 (28%)
FPG (mg/dL) | N = 256 | N = 253
Baseline (mean) | 203 | 201
Change from baseline (adjusted mean) | -63 | -40
Difference from pioglitazone (adjusted mean) (95% CI) | -23 (-30, -15)
2-hour PPG (mg/dL) | N = 216 | N = 211
Baseline (mean) | 283 | 284
Change from baseline (adjusted mean) | -114 | -69
Difference from pioglitazone (adjusted mean) (95% CI) | -45 (-57, -32)

Add-on Combination Therapy with Metformin and Rosiglitazone

A total of 278 patients with type 2 diabetes participated in a 54-week, randomized, double-blind, placebo-controlled study designed to assess the efficacy of JANUVIA in combination with metformin and rosiglitazone. Patients on dual therapy with metformin HCl ≥1500 mg/day and rosiglitazone ≥4 mg/day or with metformin HCl ≥1500 mg/day and pioglitazone ≥30 mg/day (switched to rosiglitazone ≥4 mg/day) entered a dose-stable run-in period of 6 weeks. Patients on other dual therapy were switched to metformin HCl ≥1500 mg/day and rosiglitazone ≥4 mg/day in a dose titration/stabilization run-in period of up to 20 weeks in duration. After the run-in period, patients with inadequate glycemic control (A1C 7.5% to 11%) were randomized 2:1 to the addition of either 100 mg of JANUVIA or placebo, administered once daily. Patients who failed to meet specific glycemic goals during the study were treated with glipizide (or other sulfonylurea) rescue. The primary time point for evaluation of glycemic parameters was Week 18.

In combination with metformin and rosiglitazone, JANUVIA provided significant improvements in A1C, FPG, and 2-hour PPG compared to placebo with metformin and rosiglitazone (Table 12) at Week 18. At Week 54, mean reduction in A1C was -1.0% for patients treated with JANUVIA and -0.3% for patients treated with placebo in an analysis based on the intent-to-treat population. Rescue therapy was used in 18% of patients treated with JANUVIA 100 mg and 40% of patients treated with placebo. There was no significant difference between JANUVIA and placebo in body weight change.

Table 12: Glycemic Parameters at Week 18 for JANUVIA in Add-on Combination Therapy with Metformin and Rosiglitazone [Intent-to-treat population using last observation on study prior to glipizide (or other sulfonylurea) rescue therapy.]
 | JANUVIA 100 mg + Metformin + Rosiglitazone | Placebo + Metformin + Rosiglitazone
A1C (%) | N = 176 | N = 93
Baseline (mean) | 8.8 | 8.7
Change from baseline (adjusted mean [Least squares means adjusted for prior antihyperglycemic therapy status and baseline value.]) | -1.0 | -0.4
Difference from placebo + rosiglitazone + metformin (adjusted mean) (95% CI) | -0.7 [p<0.001 compared to placebo + metformin + rosiglitazone.] (-0.9, -0.4)
Patients (%) achieving A1C <7% | 39 (22%) | 9 (10%)
FPG (mg/dL) | N = 179 | N = 94
Baseline (mean) | 181 | 182
Change from baseline (adjusted mean) | -30 | -11
Difference from placebo + rosiglitazone + metformin (adjusted mean) (95% CI) | -18 (-26, -10)
2-hour PPG (mg/dL) | N = 152 | N = 80
Baseline (mean) | 256 | 248
Change from baseline (adjusted mean) | -59 | -21
Difference from placebo + rosiglitazone + metformin (adjusted mean) (95% CI) | -39 (-51, -26)

Add-on Combination Therapy with Glimepiride, with or without Metformin

A total of 441 patients with type 2 diabetes participated in a 24-week, randomized, double-blind, placebo-controlled study designed to assess the efficacy of JANUVIA in combination with glimepiride, with or without metformin. Patients entered a run-in treatment period on glimepiride (≥4 mg per day) alone or glimepiride in combination with metformin HCl (≥1500 mg per day). After a dose-titration and dose-stable run-in period of up to 16 weeks and a 2-week placebo run-in period, patients with inadequate glycemic control (A1C 7.5% to 10.5%) were randomized to the addition of either 100 mg of JANUVIA or placebo, administered once daily. Patients who failed to meet specific glycemic goals during the studies were treated with pioglitazone rescue.

In combination with glimepiride, with or without metformin, JANUVIA provided significant improvements in A1C and FPG compared to placebo (Table 13). In the entire study population (patients on JANUVIA in combination with glimepiride and patients on JANUVIA in combination with glimepiride and metformin), a mean reduction from baseline relative to placebo in A1C of -0.7% and in FPG of -20 mg/dL was seen. Rescue therapy was used in 12% of patients treated with JANUVIA 100 mg and 27% of patients treated with placebo. In this study, patients treated with JANUVIA had a mean increase in body weight of 1.1 kg vs. placebo (+0.8 kg vs. -0.4 kg). In addition, there was an increased rate of hypoglycemia. [See Warnings and Precautions (5.4); Adverse Reactions (6.1).]

Table 13: Glycemic Parameters at Final Visit (24-Week Study) for JANUVIA as Add-On Combination Therapy with Glimepiride, with or without Metformin [Intent-to-treat population using last observation on study prior to pioglitazone rescue therapy.]
 | JANUVIA 100 mg + Glimepiride | Placebo + Glimepiride | JANUVIA 100 mg + Glimepiride + Metformin | Placebo + Glimepiride + Metformin
A1C (%) | N = 102 | N = 103 | N = 115 | N = 105
Baseline (mean) | 8.4 | 8.5 | 8.3 | 8.3
Change from baseline (adjusted mean [Least squares means adjusted for prior antihyperglycemic therapy status and baseline value.]) | -0.3 | 0.3 | -0.6 | 0.3
Difference from placebo (adjusted mean) (95% CI) | -0.6 [p<0.001 compared to placebo.] (-0.8, -0.3) |  | -0.9 (-1.1, -0.7)
Patients (%) achieving A1C <7% | 11 (11%) | 9 (9%) | 26 (23%) | 1 (1%)
FPG (mg/dL) | N = 104 | N = 104 | N = 115 | N = 109
Baseline (mean) | 183 | 185 | 179 | 179
Change from baseline (adjusted mean) | -1 | 18 | -8 | 13
Difference from placebo (adjusted mean) (95% CI) | -19 [p<0.01 compared to placebo.] (-32, -7) |  | -21 (-32, -10)

Add-on Combination Therapy with Insulin (with or without Metformin)

A total of 641 patients with type 2 diabetes participated in a 24-week, randomized, double-blind, placebo-controlled study designed to assess the efficacy of JANUVIA as add-on to insulin therapy (with or without metformin). The racial distribution in this study was approximately 70% white, 18% Asian, 7% black, and 5% other groups. Approximately 14% of the patients in this study were Hispanic. Patients entered a 2-week, single-blind run-in treatment period on pre-mixed, long-acting, or intermediate-acting insulin, with or without metformin HCl (≥1500 mg per day). Patients using short-acting insulins were excluded unless the short-acting insulin was administered as part of a pre-mixed insulin. After the run-in period, patients with inadequate glycemic control (A1C 7.5% to 11%) were randomized to the addition of either 100 mg of JANUVIA or placebo, administered once daily. Patients were on a stable dose of insulin prior to enrollment with no changes in insulin dose permitted during the run-in period. Patients who failed to meet specific glycemic goals during the double-blind treatment period were to have uptitration of the background insulin dose as rescue therapy.

The median daily insulin dose at baseline was 42 units in the patients treated with JANUVIA and 45 units in the placebo-treated patients. The median change from baseline in daily dose of insulin was zero for both groups at the end of the study. In combination with insulin (with or without metformin), JANUVIA provided significant improvements in A1C, FPG, and 2-hour PPG compared to placebo (Table 14). Both treatment groups had an adjusted mean increase in body weight of 0.1 kg from baseline to Week 24. There was an increased rate of hypoglycemia in patients treated with JANUVIA. [See Warnings and Precautions (5.4); Adverse Reactions (6.1).]

Table 14: Glycemic Parameters at Final Visit (24-Week Study) for JANUVIA as Add-on Combination Therapy with Insulin [Intent-to-treat population using last observation on study prior to rescue therapy.]
 | JANUVIA 100 mg + Insulin (+/- Metformin) | Placebo + Insulin (+/- Metformin)
A1C (%) | N = 305 | N = 312
Baseline (mean) | 8.7 | 8.6
Change from baseline (adjusted mean [Least squares means adjusted for metformin use at the screening visit (yes/no), type of insulin used at the screening visit (pre-mixed vs. non-pre-mixed [intermediate- or long-acting]), and baseline value.]) | -0.6 | -0.1
Difference from placebo (adjusted mean, [Treatment by stratum interaction was not significant (p>0.10) for metformin stratum and for insulin stratum.]) (95% CI) | -0.6 [p<0.001 compared to placebo.] (-0.7, -0.4)
Patients (%) achieving A1C <7% | 39 (12.8%) | 16 (5.1%)
FPG (mg/dL) | N = 310 | N = 313
Baseline (mean) | 176 | 179
Change from baseline (adjusted mean) | -18 | -4
Difference from placebo (adjusted mean) (95% CI) | -15 (-23, -7)
2-hour PPG (mg/dL) | N = 240 | N = 257
Baseline (mean) | 291 | 292
Change from baseline (adjusted mean) | -31 | 5
Difference from placebo (adjusted mean) (95% CI) | -36 (-47, -25)

Maintenance of JANUVIA During Initiation and Titration of Insulin Glargine

A total of 746 patients with type 2 diabetes (mean baseline HbA1C 8.8%, disease duration 10.8 years) participated in a 30-week, randomized, double-blind, placebo-controlled study to assess the efficacy and safety of continuing JANUVIA during the initiation and uptitration of insulin glargine. Patients who were on a stable dose of metformin HCl (≥1500 mg/day) in combination with a DPP-4 inhibitor and/or sulfonylurea but with inadequate glycemic control (A1C 7.5% to 11%) were enrolled in the study. Those on metformin and JANUVIA (100 mg/day) directly entered the double-blind treatment period; those on another DPP-4 inhibitor and/or on a sulfonylurea entered a 4-8 week run-in period in which they were maintained on metformin and switched to JANUVIA (100 mg); other DPP-4 inhibitors and sulfonylureas were discontinued. At randomization patients were randomized either to continue JANUVIA or to discontinue JANUVIA and switch to a matching placebo. On the day of randomization, insulin glargine was initiated at a dose of 10 units subcutaneously in the evening. Patients were instructed to uptitrate their insulin dose in the evening based on fasting blood glucose measurements to achieve a target of 72-100 mg/dL.

At 30 weeks, the mean reduction in A1C was greater in the sitagliptin group than in the placebo group (Table 15). At the end of the trial, 27.3% of patients in the sitagliptin group and 27.3% in the placebo group had a fasting plasma glucose (FPG) in the target range; there was no significant difference in insulin dose between arms.

Table 15: Change from Baseline in A1C and FPG at Week 30 in the Maintenance of JANUVIA During Initiation and Titration of Insulin Glargine Study
 | Sitagliptin 100 mg +Metformin + Insulin Glargine | Placebo +Metformin + Insulin Glargine
A1C (%) | N = 373 [N is the number of randomized and treated patients.] | N = 370
Baseline (mean) | 8.8 | 8.8
Week 30 (mean) | 6.9 | 7.3
Change from baseline (adjusted mean) [Analysis of Covariance including all post-baseline data regardless of rescue or treatment discontinuation. Model estimates calculated using multiple imputation to model washout of the treatment effect using placebo data for all subjects having missing Week 30 data.] | -1.9 | -1.4
Difference from placebo (adjusted mean) (95% CI) | -0.4 (-0.6, -0.3) [p<0.001 compared to placebo.]
Patients (%) with A1C <7% | 202 (54.2%) | 131 (35.4%)
FPG (mg/dL) | N = 373 | N = 370
Baseline (mean) | 199 | 201
Week 30 (mean) | 118 | 123
Change from baseline (adjusted mean) | -81 | -76

16 HOW SUPPLIED/STORAGE AND HANDLING

Tablets are supplied as follows:

Contents | Description | How Supplied | NDC
50 mg sitagliptin | light beige, round, film-coated tablets with “112” on one side | Bottles of approximately 2340 film-coated tablets | 55154-5040-8

Storage

Store at 20-25°C (68-77°F), excursions permitted to 15-30°C (59-86°F). [See USP Controlled Room Temperature.]

17 PATIENT COUNSELING INFORMATION

Advise the patient to read the FDA-approved patient labeling (Medication Guide).

Pancreatitis

Inform patients that acute pancreatitis has been reported during postmarketing use of JANUVIA. Inform patients that persistent severe abdominal pain, sometimes radiating to the back, which may or may not be accompanied by vomiting, is the hallmark symptom of acute pancreatitis. Instruct patients to promptly discontinue JANUVIA and contact their physician if persistent severe abdominal pain occurs [see Warnings and Precautions (5.1)].

Heart Failure

Inform patients of the signs and symptoms of heart failure. Before initiating JANUVIA, ask patients about a history of heart failure or other risk factors for heart failure including moderate to severe renal impairment. Instruct patients to contact their health care provider as soon as possible if they experience symptoms of heart failure, including increasing shortness of breath, rapid increase in weight or swelling of the feet [see Warnings and Precautions (5.2)].

Hypoglycemia

Inform patients that the incidence of hypoglycemia is increased when JANUVIA is added to a sulfonylurea or insulin. Explain to patients receiving JANUVIA in combination with these medications the risks of hypoglycemia, its symptoms and treatment, and conditions that predispose to its development [see Warnings and Precautions (5.4)].

Hypersensitivity Reactions

Inform patients that allergic reactions have been reported during postmarketing use of JANUVIA. If symptoms of allergic reactions (including rash, hives, and swelling of the face, lips, tongue, and throat that may cause difficulty in breathing or swallowing) occur, patients must stop taking JANUVIA and seek medical advice promptly [see Warnings and Precautions (5.5)].

Severe and Disabling Arthralgia

Inform patients that severe and disabling joint pain may occur with this class of drugs. The time to onset of symptoms can range from one day to years. Instruct patients to seek medical advice if severe joint pain occurs [see Warnings and Precautions (5.6)].

Bullous Pemphigoid

Inform patients that bullous pemphigoid may occur with this class of drugs. Instruct patients to seek medical advice if blisters or erosions occur [see Warnings and Precautions (5.7)].

Distributed by: Merck Sharp & Dohme LLC
Rahway, NJ 07065, USA

For patent information: www.msd.com/research/patent

Copyright © 2006-2023 Merck & Co., Inc., Rahway, NJ, USA, and its affiliates.
All rights reserved.

Distributed By:

Cardinal Health

Dublin, OH 43017

ER7305 Rev. B

uspi-mk0431-t-2307r029

Medication Guide
JANUVIA® (jah-NEW-vee-ah)
(sitagliptin)
tablets, for oral use

Read this Medication Guide carefully before you start taking JANUVIA and each time you get a refill. There may be new information. This information does not take the place of talking with your doctor about your medical condition or your treatment. If you have any questions about JANUVIA, ask your doctor or pharmacist.

What is the most important information I should know about JANUVIA?
JANUVIA can cause serious side effects, including:

- Inflammation of the pancreas (pancreatitis) which may be severe and lead to death. Certain medical problems make you more likely to get pancreatitis.
  Before you start taking JANUVIA, tell your doctor if you have ever had:

- pancreatitis
- high blood triglyceride levels

- stones in your gallbladder (gallstones)
- kidney problems

- a history of alcoholism

Stop taking JANUVIA and call your doctor right away if you have pain in your stomach area (abdomen) that is severe and will not go away. The pain may be felt going from your abdomen through to your back. The pain may happen with or without vomiting. These may be symptoms of pancreatitis.

- Heart failure. Heart failure means your heart does not pump blood well enough.
  Before you start taking JANUVIA, tell your doctor if you have ever had heart failure or have problems with your kidneys. Contact your doctor right away if you have any of the following symptoms:

- increasing shortness of breath or trouble breathing, especially when you lie down
- swelling or fluid retention, especially in the feet, ankles or legs
- an unusually fast increase in weight
- unusual tiredness

These may be symptoms of heart failure.

What is JANUVIA?

- JANUVIA is a prescription medicine used along with diet and exercise to lower blood sugar in adults with type 2 diabetes.
- JANUVIA is not for people with type 1 diabetes.
- If you have had pancreatitis (inflammation of the pancreas) in the past, it is not known if you have a higher chance of getting pancreatitis while you take JANUVIA.
- The safety and effectiveness of JANUVIA have not been established in pediatric patients.

Who should not take JANUVIA?
Do not take JANUVIA if:

- you are allergic to any of the ingredients in JANUVIA. See the end of this Medication Guide for a complete list of ingredients in JANUVIA.

Symptoms of a serious allergic reaction to JANUVIA may include rash, raised red patches on your skin (hives), or swelling of the face, lips, tongue, and throat that may cause difficulty in breathing or swallowing.

What should I tell my doctor before taking JANUVIA?
Before you take JANUVIA, tell your doctor about all of your medical conditions, including if you:

- have or have had inflammation of your pancreas (pancreatitis).
- have kidney problems.
- have heart failure.
- are pregnant or plan to become pregnant. It is not known if JANUVIA will harm your unborn baby. If you are pregnant, talk with your doctor about the best way to control your blood sugar while you are pregnant.
- are breastfeeding or plan to breastfeed. It is not known if JANUVIA will pass into your breast milk. Talk with your doctor about the best way to feed your baby if you are taking JANUVIA.

Tell your doctor about all the medicines you take, including prescription and over-the-counter medicines, vitamins, and herbal supplements.
Know the medicines you take. Keep a list of your medicines and show it to your doctor and pharmacist when you get a new medicine.

How should I take JANUVIA?

- Take JANUVIA 1 time each day exactly as your doctor tells you.
- You can take JANUVIA with or without food.
- Your doctor will do blood tests to check how well your kidneys are working before and during your treatment with JANUVIA.
- Your doctor may tell you to take JANUVIA along with other diabetes medicines. Low blood sugar can happen more often when JANUVIA is taken with certain other diabetes medicines. See "What are the possible side effects of JANUVIA?".
- If you miss a dose, take it as soon as you remember. If you do not remember until it is time for your next dose, skip the missed dose and go back to your regular schedule. Do not take two doses of JANUVIA at the same time.
- If you take too much JANUVIA, call your doctor or local Poison Control Center right away.
- When your body is under some types of stress, such as fever, trauma (such as a car accident), infection or surgery, the amount of diabetes medicine that you need may change. Tell your doctor right away if you have any of these conditions and follow your doctor's instructions.
- Check your blood sugar as your doctor tells you to.
- Stay on your prescribed diet and exercise program while taking JANUVIA.
- Talk to your doctor about how to prevent, recognize and manage low blood sugar (hypoglycemia), high blood sugar (hyperglycemia), and problems you have because of your diabetes.
- Your doctor will check your diabetes with regular blood tests, including your blood sugar levels and your hemoglobin A1C.

What are the possible side effects of JANUVIA?
JANUVIA may cause serious side effects, including:

- See "What is the most important information I should know about JANUVIA?".
- Kidney problems, sometimes requiring dialysis.
- Low blood sugar (hypoglycemia). If you take JANUVIA with another medicine that can cause low blood sugar, such as a sulfonylurea or insulin, your risk of getting low blood sugar is higher. The dose of your sulfonylurea medicine or insulin may need to be lowered while you use JANUVIA. Signs and symptoms of low blood sugar may include:

- headache
- drowsiness

- irritability
- hunger

- dizziness
- confusion

- sweating
- feeling jittery

- weakness
- fast heart beat

- Serious allergic reactions. If you have any symptoms of a serious allergic reaction, stop taking JANUVIA and call your doctor right away or get emergency medical help. See "Who should not take JANUVIA?". Your doctor may give you a medicine for your allergic reaction and prescribe a different medicine for your diabetes.
- Joint pain. Some people who take medicines called DPP-4 inhibitors like JANUVIA, may develop joint pain that can be severe. Call your doctor if you have severe joint pain.
- Skin reaction. Some people who take medicines called DPP-4 inhibitors like JANUVIA may develop a skin reaction called bullous pemphigoid that can require treatment in a hospital. Tell your doctor right away if you develop blisters or the breakdown of the outer layer of your skin (erosion). Your doctor may tell you to stop taking JANUVIA.

The most common side effects of JANUVIA include upper respiratory infection, stuffy or runny nose and sore throat, and headache.
JANUVIA may have other side effects, including stomach upset and diarrhea, swelling of the hands or legs, when JANUVIA is used with metformin and rosiglitazone (Avandia). Rosiglitazone is another type of diabetes medicine.
Tell your doctor if you have any side effect that bothers you or does not go away.
These are not all the possible side effects of JANUVIA. For more information, ask your doctor or pharmacist.
Call your doctor for medical advice about side effects. You may report side effects to FDA at 1-800-FDA-1088.

How should I store JANUVIA?
Store JANUVIA at room temperature, between 68°F to 77°F (20°C to 25°C).
Keep JANUVIA and all medicines out of the reach of children.

General information about the safe and effective use of JANUVIA.
Medicines are sometimes prescribed for purposes other than those listed in a Medication Guide. Do not use JANUVIA for a condition for which it was not prescribed. Do not give JANUVIA to other people, even if they have the same symptoms you have. It may harm them.
This Medication Guide summarizes the most important information about JANUVIA. If you would like to know more information, talk with your doctor. You can ask your doctor or pharmacist for information about JANUVIA that is written for health professionals.

What are the ingredients in JANUVIA?
Active ingredient: sitagliptin
Inactive ingredients: microcrystalline cellulose, anhydrous dibasic calcium phosphate, croscarmellose sodium, magnesium stearate, sodium stearyl fumarate, and propyl gallate. The tablet film coating contains the following inactive ingredients: polyvinyl alcohol, polyethylene glycol, talc, titanium dioxide, red iron oxide, and yellow iron oxide.

Distributed by: Merck Sharp & Dohme LLC
Rahway, NJ 07065, USA
For more information, go to www.JANUVIA.com or call 1-800-622-4477.
For patent information: www.msd.com/research/patent. The trademarks depicted herein are owned by their respective companies. Copyright © 2010-2023 Merck & Co., Inc., Rahway, NJ, USA, and its affiliates.
All rights reserved.

Distributed By:

Cardinal Health

Dublin, OH 43017

ER7305 Rev. B

usmg-mk0431-t-2307r020

This Medication Guide has been approved by the U.S. Food and Drug Administration.

Revised: 07/2023

Package/Label Display Panel

Contains Approximately

2340 Tablets

JANUVIA®

(sitagliptin) tablets

50 mg

Each tablet contains:

64.25 mg sitagliptin phosphate,

equivalent to 50 mg sitagliptin.

Rx Only

WARNING: Keep out of reach of

children.